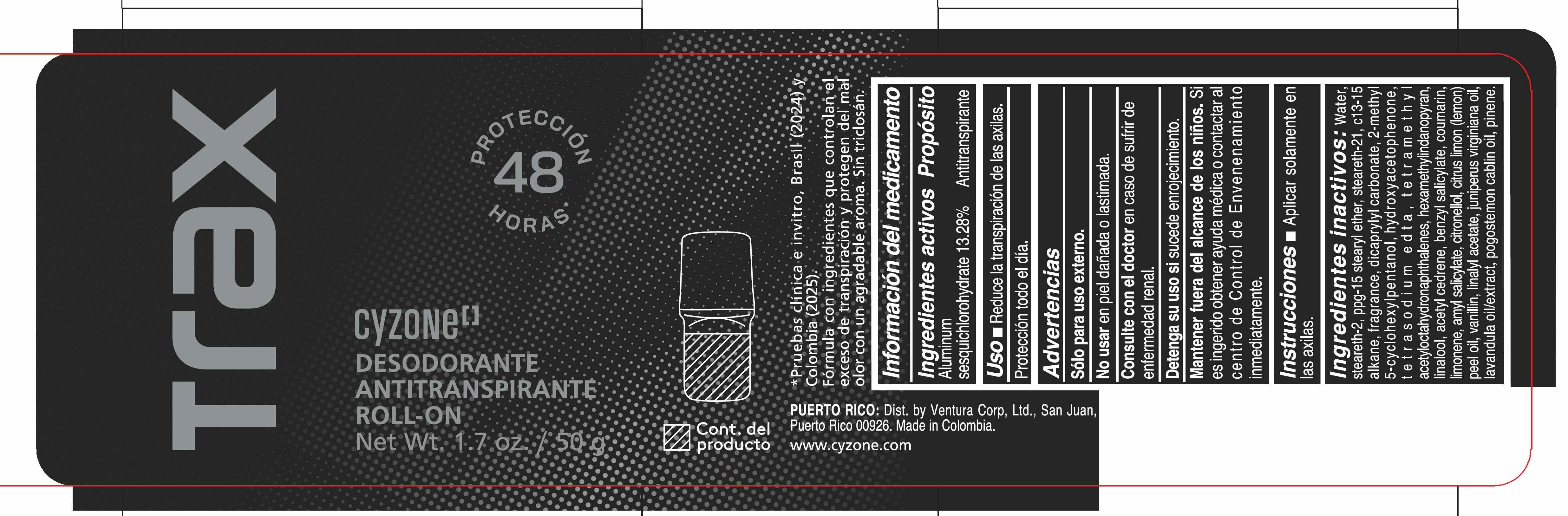 DRUG LABEL: CYZONE TRAX DESODORANTE ANTITRANSPIRANTE ROLL ON
NDC: 14141-458 | Form: EMULSION
Manufacturer: BEL STAR SA
Category: otc | Type: HUMAN OTC DRUG LABEL
Date: 20251202

ACTIVE INGREDIENTS: ALUMINUM SESQUICHLOROHYDRATE 132.8 mg/1 g
INACTIVE INGREDIENTS: LINALOOL; STEARETH-2; TETRASODIUM EDTA; CITRUS LIMON (LEMON) PEEL OIL; JUNIPERUS VIRGINIANA OIL; STEARETH-21; 2-METHYL 5-CYCLOHEXYLPENTANOL; COUMARIN; LIMONENE, (+)-; HYDROXYACETOPHENONE; BENZYL SALICYLATE; POGOSTEMON CABLIN OIL; LAVENDER OIL; WATER; PPG-15 STEARYL ETHER; C13-15 ALKANE; TETRAMETHYL ACETYLOCTAHYDRONAPHTHALENES; HEXAMETHYLINDANOPYRAN; DICAPRYLYL CARBONATE; ACETYL CEDRENE; CITRONELLOL; VANILLIN; PINENE; LINALYL ACETATE; AMYL SALICYLATE

CYZONE TRAX DESODORANTE ANTITRANSPIRANTE ROLL ON

Ingredientes activos

Aluminum sesquichlorohydrate 13.28%

Proposito

Antitranspirante

Uso

- Reduce la transpiracion de las axilas.
- Proteccion todo el dia.

Advertencias

Solo para uso externo.

No usar

en piel danada o lastimada.

Consulte con el doctor

en caso de sufrir de enfermedad renal.

Detenga su uso si

sucede enrojecimiento.

Mantener fuera del alcance de los ninos.

Si es ingerido obtener ayuda medica o contactar al centro de Control de Envenenamiento inmediatamente.

Instrucciones

- Aplicar solamente en las axilas.

Ingredientes inactivos

Water, steareth-2, ppg-15 stearyl ether, steareth-21, c13-15 alkane, fragrance, dicaprylyl carbonate, 2-methyl 5-cyclohexylpentanol, hydroxyacetophenone, tetrasodium edta, tetramethyl acetyloctahydronaphthalenes, hexamethylindanopyran, linalool, acetyl cedrene, benzyl salicylate, coumarin, limonene, amyl salicylate, citronellol, citrus limon (lemon) peel oil, vanillin, linalyl acetate, juniperus virginiana oil, lavandula oil/extract, pogostemon cablin oil, pinene.